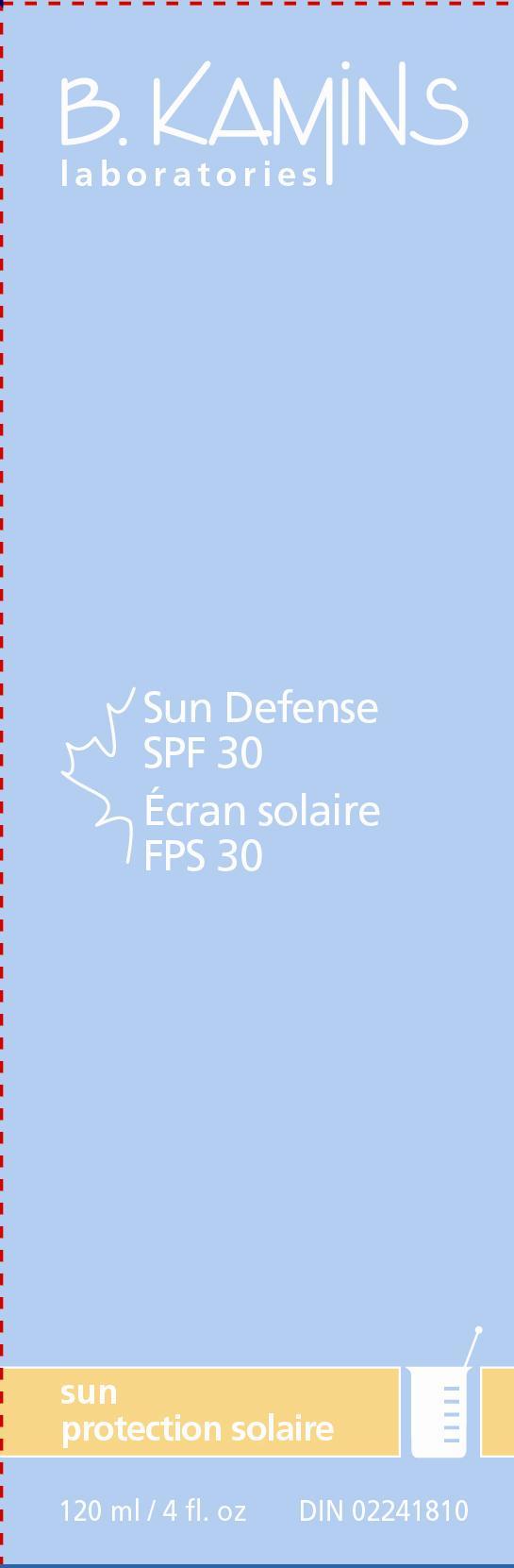 DRUG LABEL: SUN DEFENSE SPF 30
NDC: 63550-851 | Form: LOTION
Manufacturer: Kamins Dermatologics Inc.
Category: otc | Type: HUMAN OTC DRUG LABEL
Date: 20110902

ACTIVE INGREDIENTS: AVOBENZONE 25 mg/1 mL; OCTINOXATE 75 mg/1 mL; OXYBENZONE 6 mg/1 mL; TITANIUM DIOXIDE 20 mg/1 mL
INACTIVE INGREDIENTS: WATER; OCTYLDODECYL NEOPENTANOATE; PROPYLENE GLYCOL; ACER SACCHARUM SAP; .ALPHA.-TOCOPHEROL ACETATE, D-; CETYL ALCOHOL; STEARIC ACID; DIETHANOLAMINE CETYL PHOSPHATE; PANTHENOL; DIMETHICONE; XANTHAN GUM; SODIUM HYDROXIDE; PHENOXYETHANOL; CHLORPHENESIN; BUTYLATED HYDROXYTOLUENE; FERRIC OXIDE RED

SUN DEFENSE SPF30 CONSUMER LABELING

Active ingredients:

Avobenzone 2.5%

Octinoxate 7.5%

Oxybenzone 6%

Titanium dioxide 2%

Purpose: Sunscreen

Keep out of reach of children.

INDICATIONS AND USAGE

This oil and fragrance-free broad spectrum UVA/UVB sunscreen provides important protection against the sun’s harmful rays. Recommended for use on face and body, for everyday wear and outdoor activities. This cosmetically elegant formula is non-greasy, leaves a matte finish, and can be reapplied over makeup.

• fragrance-free • oil-free
• for face and body

Uses
■ Helps prevent sunburn.

■ Higher SPF gives more sunburn protection.

■ Provides high protection against sunburn.

Warnings
For external use only.
When using this product, keep out of eyes. If contact occurs, rinse abundantly with water to remove.
Stop use and ask a doctor if rash or irritation develops and lasts.
If swallowed, seek medical assistance or contact a Poison Control Center immediately.

Other information

Sun alert: Limiting sun exposure, wearing protective clothing, and using sunscreens may reduce the risks of skin aging, skin cancer, and other harmful effects of the sun.

Store at room temperature 15-30°C (59-86°F).

Directions
■ Apply liberally and evenly to face and exposed areas 15-30 minutes before sun exposure.

■ Reapply every two hours or as needed.

■ Reapply after swimming, towel drying, washing or perspiring heavily.

■ Children under 6 months of age: ask a doctor.

INACTIVE INGREDIENT

Inactive ingredients: water, octyldodecyl neopentanoate, propylene glycol, acer saccharum, tocopheryl acetate, cetyl alcohol, stearic acid, DEA-cetyl phosphate, panthenol, dimethicone, xanthan gum, carbomer, sodium hydroxide, phenoxyethanol, chlorphenesin, BHT, iron oxides (CI 77491).

PACKAGE LABEL

SUN DEFENSE SPF 30
120 mL / 4 fl. oz
DIN 02241810
image/jpg